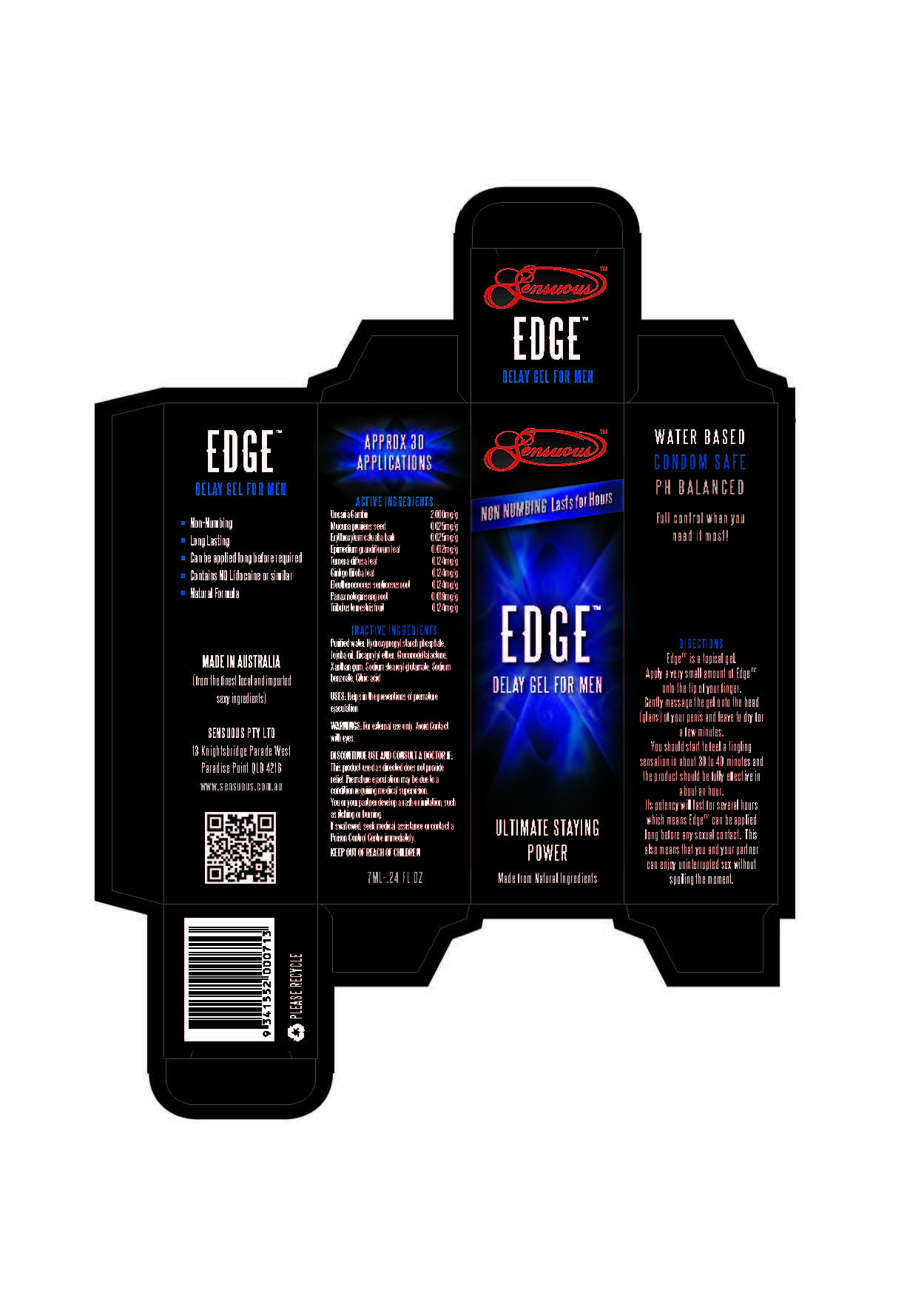 DRUG LABEL: Edge
                
NDC: 69768-001 | Form: GEL
Manufacturer: Sensuous Pty Ltd
Category: otc | Type: HUMAN OTC DRUG LABEL
Date: 20150417

ACTIVE INGREDIENTS: GAMBIR 2 mg/1 g; MUCUNA PRURIENS SEED .025 mg/1 g; ERYTHROXYLUM CATUABA BARK  .025 mg/1 g; EPIMEDIUM GRANDIFLORUM TOP .012 mg/1 g; TURNERA DIFFUSA LEAF .124 mg/1 g; GINKGO .124 mg/1 g; ELEUTHERO .124 mg/1 g; PANAX NOTOGINSENG ROOT .018 mg/1 g; TRIBULUS TERRESTRIS FRUIT .124 mg/1 g
INACTIVE INGREDIENTS: WATER; JOJOBA OIL; DICAPRYLYL ETHER; GLUCONOLACTONE; XANTHAN GUM; SODIUM STEAROYL GLUTAMATE; SODIUM BENZOATE; CITRIC ACID MONOHYDRATE

Drug Facts

Active Ingredients

Uncaria Gambir 2.000 mg/g

Mucuna pruriens seed 0.025 mg/g

Erythroxylum catuaba bark 0.025 mg/g

Epimedium grandiflorum leaf 0.012 mg/g

Turnera diffusa leaf 0.124 mg/g

Ginkgo Biloba leaf 0.124 mg/g

Eluetherococcus senticosus root 0.124 mg/g

Panax notoginseng root 0.018 mg/g

Tribulus terrestris fruit 0.124 mg/g

Inactive Ingredients

Purified water, Hydroxypropyl starch phosphate,

Jojoba oil, Dicaprylyl ether, Gluconodeltalactone,

Xanthan gum, Sodium stearoyl glutamate, Sodium

benzoate, Citric acid

PURPOSE

Delay gel for men

WARNINGS

Warnings: For external use only. Avoid Contact with eyes

INDICATIONS AND USAGE

Uses: Helps in the preventions of premature ejaculation

Discontinue Use and Consult a Doctor if:

This product used as directed does not provide

relief. Premature ejaculation may be due to a condition

requiring medical supervision.

You or your partner may develop a rash or irritation, such

as itching or burning.

If swallowed, seek medical assistance or contact

a Poison Control Center immediately.

KEEP OUT OF REACH OF CHILDREN.

Directions

Edge is a topical gel. Apply a very small amount

of Edge onto the tip of your finger.

Gently massage the gel onto the head

(glans) of your penis and leave to air dry for

a few minutes.

You should start to feel a tingling sensation in about

30 to 40 minutes and the product should be fully effective

in about an hour.

Its potency will last several hours which means Edge can be

applied long before any sexual contact. This also means that

you and your partner can enjoy uninterrupted sex without

spoiling the moment.